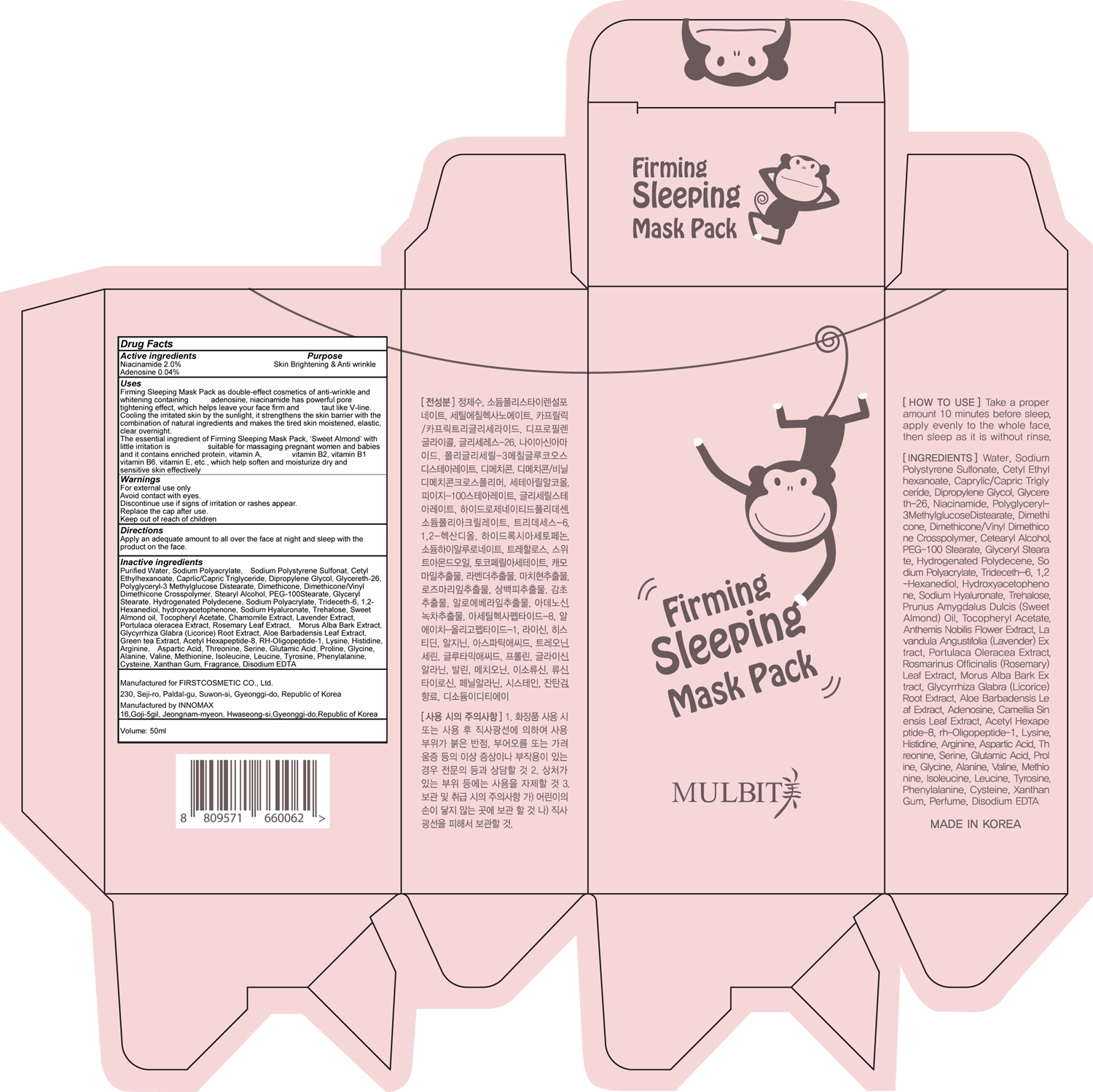 DRUG LABEL: MULBIT ME FIRMING SLEEPING PACK
NDC: 71635-100 | Form: CREAM
Manufacturer: First Cosmetic Co., Ltd
Category: otc | Type: HUMAN OTC DRUG LABEL
Date: 20171116

ACTIVE INGREDIENTS: Niacinamide 1.00 g/50 mL; Adenosine 0.02 g/50 mL
INACTIVE INGREDIENTS: Water; Cetyl Ethylhexanoate

ACTIVE INGREDIENT

Active ingredients: Niacinamide 2.0%, Adenosine 0.04%

INACTIVE INGREDIENT

Inactive ingredients: Purified Water, Sodium Polyacrylate, Sodium Polystyrene Sulfonat, Cetyl Ethylhexanoate, Caprlic/Capric Triglyceride, Dipropylene Glycol, Glycereth-26, Polyglyceryl-3 Methylglucose Distearate, Dimethicone, Dimethicone/Vinyl Dimethicone Crosspolymer, Stearyl Alcohol, PEG-100Stearate, Glyceryl Stearate, Hydrogenated Polydecene, Sodium Polyacrylate, Trideceth-6, 1,2-Hexanediol, hydroxyacetophenone, Sodium Hyaluronate, Trehalose, Sweet Almond oil, Tocopheryl Acetate, Chamomile Extract, Lavender Extract, Portulaca oleracea Extract, Rosemary Leaf Extract, Morus Alba Bark Extract, Glycyrrhiza Glabra (Licorice) Root Extract, Aloe Barbadensis Leaf Extract, Green tea Extract, Acetyl Hexapeptide-8, RH-Oligopeptide-1, Lysine, Histidine, Arginine, Aspartic Acid, Threonine, Serine, Glutamic Acid, Proline, Glycine, Alanine, Valine, Methionine, Isoleucine, Leucine, Tyrosine, Phenylalanine, Cysteine, Xanthan Gum, Fragrance, Disodium EDTA

PURPOSE

Purpose: Skin Brightening & Anti wrinkle

WARNINGS

Warnings: For external use only Avoid contact with eyes. Discontinue use if signs of irritation or rashes appear. Replace the cap after use. Keep out of reach of children

KEEP OUT OF REACH OF CHILDREN

Uses

Uses: Firming Sleeping Mask Pack as double-effect cosmetics of anti-wrinkle and whitening containing adenosine, niacinamide has powerful pore tightening effect, which helps leave your face firm and taut like V-line. Cooling the irritated skin by the sunlight, it strengthens the skin barrier with the combination of natural ingredients and makes the tired skin moistened, elastic, clear overnight. The essential ingredient of Firming Sleeping Mask Pack, ‘Sweet Almond’ with little irritation is suitable for massaging pregnant women and babies and it contains enriched protein, vitamin A, vitamin B2, vitamin B1 vitamin B6, vitamin E, etc., which help soften and moisturize dry and sensitive skin effectively

Directions

Directions: Apply an adequate amount to all over the face at night and sleep with the product on the face.